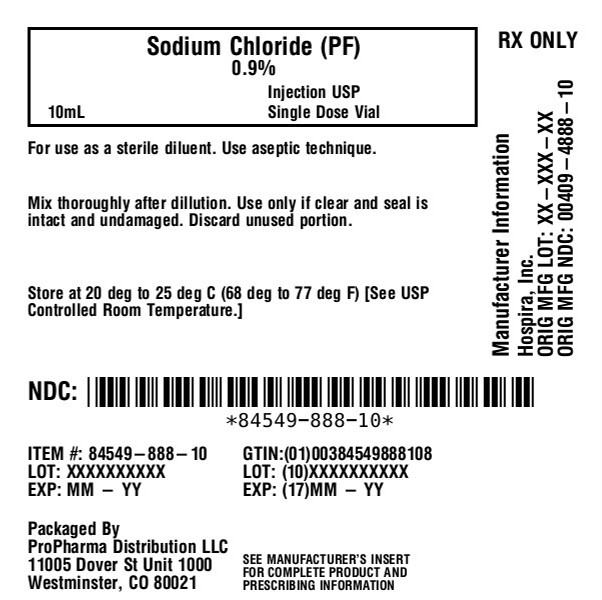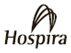 DRUG LABEL: Sodium Chloride
NDC: 84549-888 | Form: INJECTION, SOLUTION
Manufacturer: ProPharma Distribution
Category: prescription | Type: HUMAN PRESCRIPTION DRUG LABEL
Date: 20260120

ACTIVE INGREDIENTS: SODIUM CHLORIDE 9 mg/1 mL
INACTIVE INGREDIENTS: WATER; HYDROCHLORIC ACID; SODIUM HYDROXIDE

0.9% Sodium Chloride

Injection, USP

Carpuject™ with Luer Lock
Fliptop Plastic Vial
LifeShield® Fliptop Plastic Vial

Preservative-Free

Rx only

DESCRIPTION

This preparation is designed solely for parenteral use only after addition of drugs that require dilution or must be dissolved in an aqueous vehicle prior to injection.

0.9% Sodium Chloride Injection, USP is a sterile, nonpyrogenic, isotonic solution of sodium chloride and water for injection. Each mL contains sodium chloride 9 mg. It contains no bacteriostat, antimicrobial agent or added buffer and is supplied only in single-dose containers to dilute or dissolve drugs for injection. 0.308 mOsmol/mL (calc.). 0.9% Sodium Chloride Injection, USP contains no preservatives. The solution may contain hydrochloric acid and/or sodium hydroxide for pH adjustment. pH 5.3 (4.5 to 7.0).

Sodium Chloride, USP is chemically designated NaCl, a white crystalline compound freely soluble in water.

The glass container is a Type I borosilicate glass and meets the requirements of the powdered glass test according to the USP standards.

The semi-rigid vial is fabricated from a specially formulated polyolefin. It is a copolymer of ethylene and propylene. The safety of the plastic has been confirmed by tests in animals according to USP biological standards for plastic containers. The container requires no vapor barrier to maintain the proper drug concentration.

CLINICAL PHARMACOLOGY

Sodium chloride in water dissociates to provide sodium (Na^+) and chloride (Cl‾) ions. These ions are normal constituents of the body fluids (principally extracellular) and are essential for maintaining electrolyte balance.

The distribution and excretion of sodium (Na^+) and chloride (Cl‾) are largely under the control of the kidney which maintains a balance between intake and output.

The small volume of fluid and amount of sodium chloride provided by 0.9% Sodium Chloride Injection, USP when used only as an isotonic vehicle for parenteral injection of drugs, is unlikely to exert a significant effect on fluid and electrolyte balance except possibly in neonates and very small infants.

Water is an essential constituent of all body tissues and accounts for approximately 70% of total body weight. Average normal adult daily requirement ranges from two to three liters (1.0 to 1.5 liters each for insensible water loss by perspiration and urine production).

Water balance is maintained by various regulatory mechanisms. Water distribution depends primarily on the concentration of electrolytes in the body compartments and sodium (Na^+) plays a major role in maintaining physiologic equilibrium.

INDICATIONS AND USAGE

This parenteral preparation is indicated only for diluting or dissolving drugs for intravenous, intramuscular or subcutaneous injection, according to instructions of the manufacturer of the drug to be administered.

PRECAUTIONS

Consult the manufacturer's instructions for choice of vehicle, appropriate dilution or volume for dissolving the drugs to be injected, including the route and rate of injection.

Inspect reconstituted (diluted or dissolved) drugs for clarity (if soluble) and freedom from unexpected precipitation or discoloration prior to administration.

Pregnancy:Animal reproduction studies have not been conducted with 0.9% Sodium Chloride Injection, USP. It is also not known whether sodium chloride injection containing additives can cause fetal harm when administered to a pregnant woman or can affect reproduction capacity. Sodium chloride injection containing additives should be given to a pregnant woman only if clearly needed.

Pediatric Use:The safety and effectiveness in the pediatric population are based on the similarity of the clinical conditions of the pediatric and adult populations. In neonates or very small infants the volume of fluid may affect fluid and electrolyte balance.

Drug Interactions

Some drugs for injection may be incompatible in a given vehicle, or when combined in the same vehicle or in a vehicle containing benzyl alcohol. Consult with pharmacist, if available.

Use aseptic technique for single or multiple entry and withdrawal from all containers.

When diluting or dissolving drugs, mix thoroughly and use promptly.

Do not store reconstituted solutions of drugs for injection unless otherwise directed by the manufacturer of the solute.

Do not use unless the solution is clear and seal intact. Do not reuse single-dose containers, discard unused portion.

ADVERSE REACTIONS

Reactions which may occur because of this solution, added drugs or the technique of reconstitution or administration include febrile response, local tenderness, abscess, tissue necrosis or infection at the site of injection, venous thrombosis or phlebitis extending from the site of injection and extravasation.

If an adverse reaction does occur, discontinue the infusion, evaluate the patient, institute appropriate countermeasures, and if possible, retrieve and save the remainder of the unused vehicle for examination.

OVERDOSAGE

Use only as a diluent or solvent. This parenteral preparation is unlikely to pose a threat of carbohydrate, sodium chloride or fluid overload except possibly in neonates or very small infants. In the event these should occur, re-evaluate the patient and institute appropriate corrective measures. See PRECAUTIONSand ADVERSE REACTIONS.

DOSAGE AND ADMINISTRATION

The volume of the preparation to be used for diluting or dissolving any drug for injection, is dependent on the vehicle concentration, dose and route of administration as recommended by the manufacturer. This parenteral should be inspected visually for particulate matter and discoloration prior to administration, whenever solution and container permit.

HOW SUPPLIED

0.9% Sodium Chloride Injection, USP is supplied in the following:

Unit of Sale | Concentration
NDC 84549-888-10 Single-dose Plastic Fliptop Vial | 0.9% (10 mL)

Store at 20 to 25°C (68 to 77°F) [See USP Controlled Room Temperature.]

Instructions for Use of the Syringe Systems

Instructions for using the Carpuject Syringe are available with the reusable Carpuject Holder, List 2049-02.

LIFESHIELD®is the trademark of ICU Medical, Inc. and is used under license.